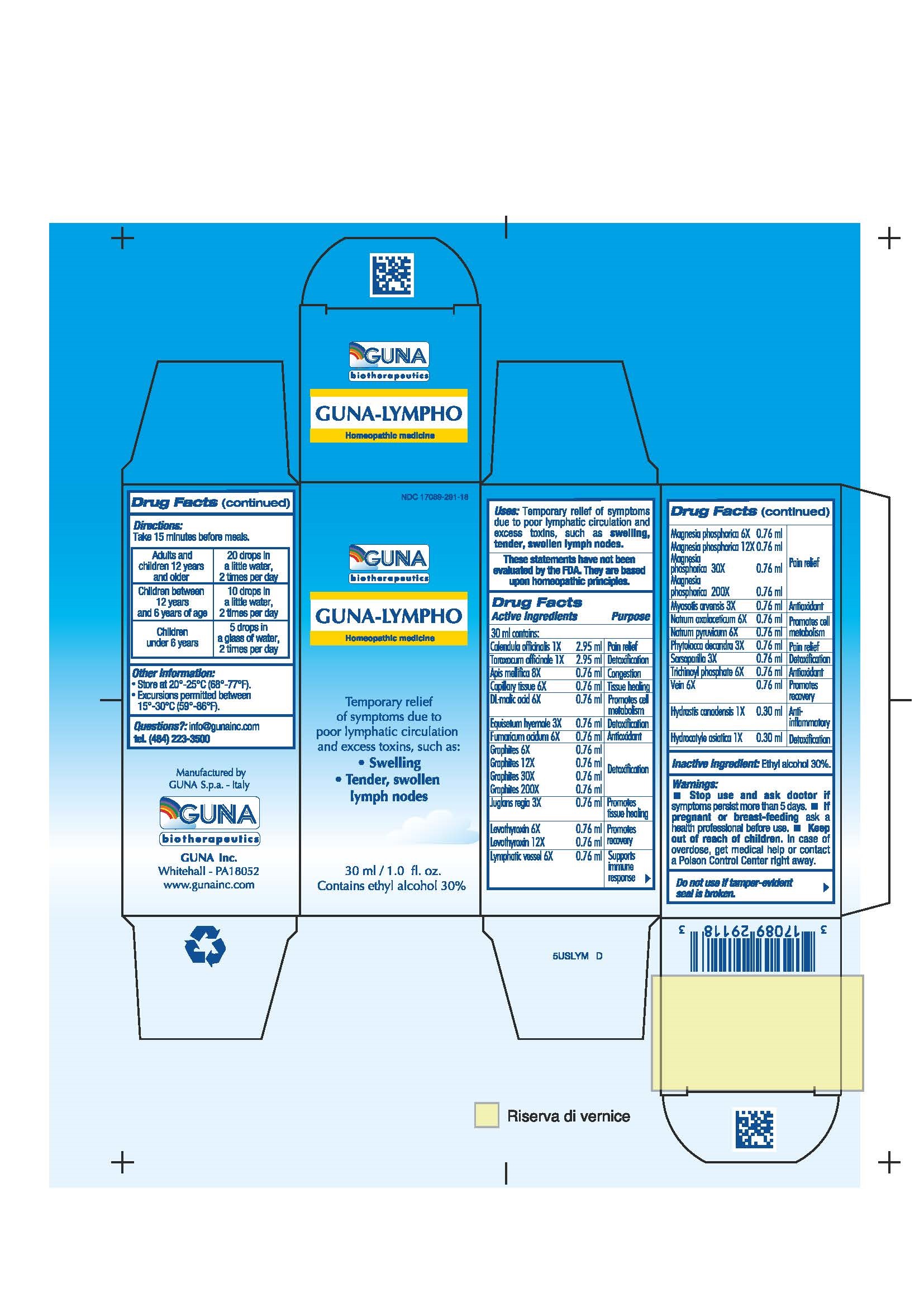 DRUG LABEL: GUNA-LYMPHO
NDC: 17089-291 | Form: SOLUTION/ DROPS
Manufacturer: Guna spa
Category: homeopathic | Type: HUMAN OTC DRUG LABEL
Date: 20221114

ACTIVE INGREDIENTS: APIS MELLIFERA 8 [hp_X]/30 mL; CALENDULA OFFICINALIS FLOWER 1 [hp_X]/30 mL; SUS SCROFA CAPILLARY TISSUE 6 [hp_X]/30 mL; MALIC ACID 6 [hp_X]/30 mL; EQUISETUM HYEMALE 3 [hp_X]/30 mL; FUMARIC ACID 6 [hp_X]/30 mL; GRAPHITE 30 [hp_X]/30 mL; GOLDENSEAL 1 [hp_X]/30 mL; CENTELLA ASIATICA 1 [hp_X]/30 mL; JUGLANS REGIA LEAF 3 [hp_X]/30 mL; LEVOTHYROXINE 12 [hp_X]/30 mL; SUS SCROFA SMALL INTESTINE MUCOSA LYMPH FOLLICLE 6 [hp_X]/30 mL; MAGNESIUM PHOSPHATE, TRIBASIC, PENTAHYDRATE 6 [hp_X]/30 mL; MYOSOTIS ARVENSIS 3 [hp_X]/30 mL; SODIUM DIETHYL OXALACETATE 6 [hp_X]/30 mL; SODIUM PYRUVATE 6 [hp_X]/30 mL; PHYTOLACCA AMERICANA ROOT 3 [hp_X]/30 mL; SARSAPARILLA 3 [hp_X]/30 mL; TARAXACUM OFFICINALE 1 [hp_X]/30 mL; DODECAHYDROXYCYCLOHEXANE DIHYDRATE 6 [hp_X]/30 mL; SUS SCROFA VEIN 6 [hp_X]/30 mL
INACTIVE INGREDIENTS: ALCOHOL 9 mL/30 mL

GUNA-LYMPHO

ACTIVE INGREDIENTS/PURPOSE

APIS MELLIFICA 8X CONGESTION
CALENDULA OFFICINALIS 1X PAIN RELIEF
CAPILLARY TISSUE 6X TISSUE HEALING
DL-MALIC ACID 6X PROMOTES CELL METABOLISM
EQUISETUM HYEMALE 3X DETOXIFICATION
FUMARICUM ACIDUM 6X ANTIOXIDANT
GRAPHITES 6X 12X 30X 200X DETOXIFICATION
HYDRASTIS CANADENSIS 1X ANTI-INFLAMMATORY
HYDROCOTYLE ASIATICA 1X DETOXIFICATION
JUGLANS REGIA 3X PROMOTES TISSUE HEALING
LEVOTHYROXIN 6X 12X PROMOTES RECOVERY
LYMPHATIC VESSEL 6X SUPPORTS IMMUNE RESPONSE
MAGNESIA PHOSPHORICA 6X 12X 30X 200X PAIN RELIEF
MYOSOTIS ARVENSIS 3X ANTIOXIDANT
NATRUM OXALACETICUM 6X PROMOTES CELL METABOLISM
NATRUM PYRUVICUM 6X PROMOTES CELL METABOLISM
PHYTOLACCA DECANDRA 3X PAIN RELIEF
SARSAPARILLA 3X DETOXIFICATION
TARAXACUM OFFICINALE 1X DETOXIFICATION
TRICHINOYL PHOSPHATE 6X ANTIOXIDANT
VEIN 6X PROMOTES RECOVERY

USES

Temporary relief of symptoms due to poor lymphatic circulation and excess toxins, such as:

- Swelling
- Tender, swollen lymph nodes

WARNINGS

- Stop use and ask doctor if symptoms persist more than 5 days.
- If pregnant or breast-feeding ask a health professional before use.
- Keep out of reach of children. In case of overdose, get medical help or contact a Poison Control Center right away.
- Contains ethyl alcohol 30%

PREGNANCY

If pregnant or breast-feeding ask a doctor before use

WARNINGS

Keep out of reach of children

DIRECTIONS

Adults and children 12 years and older 20 drops in a little water, 2 times per day
Children between 12 years and 6 years of age 10 drops in a little water, 2 times per day
Children under 6 years 5 drops in a glass of water, 2 times per day

QUESTIONS

Questions?: info@gunainc.com, tel. (484) 223-3500

INDICATIONS AND USAGE

Take 15 minutes before meals

Inactive ingredient: Ethyl alcohol 30%.